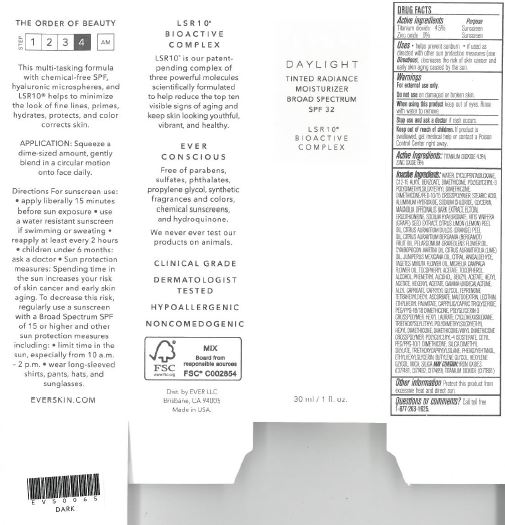 DRUG LABEL: Dark Daylight Tinted Radiance Moisturizer Broad Spectrum SPF 32
NDC: 62742-4150 | Form: CREAM
Manufacturer: Allure Labs Inc
Category: otc | Type: HUMAN OTC DRUG LABEL
Date: 20171208

ACTIVE INGREDIENTS: ZINC OXIDE 60 mg/1 mL; TITANIUM DIOXIDE 45 mg/1 mL
INACTIVE INGREDIENTS: WATER; CYCLOMETHICONE 5; ALKYL (C12-15) BENZOATE; DIMETHICONE; STEARIC ACID; ALUMINUM HYDROXIDE; SODIUM CHLORIDE; GLYCERIN; MAGNOLIA OFFICINALIS BARK; ECTOINE; ERGOTHIONEINE; CAPRYLYL GLYCOL; TEPRENONE; HYALURONATE SODIUM; VITIS VINIFERA SEED; CITRUS LIMON FRUIT OIL; TETRAHEXYLDECYL ASCORBATE; CITRUS AURANTIUM FRUIT OIL; CYMBOPOGON MARTINI TOP; PELARGONIUM GRAVEOLENS FLOWER OIL; CITRUS AURANTIIFOLIA FRUIT OIL; TOCOPHEROL; CITRAL; O-ANISALDEHYDE; ETHYLHEXYL PALMITATE; TAGETES MINUTA FLOWER OIL; MICHELIA CHAMPACA FLOWER; ALCOHOL; BENZYL ACETATE; MALTODEXTRIN; MEDIUM-CHAIN TRIGLYCERIDES; PEG/PPG-18/18 DIMETHICONE; HEXYL LAURATE; CYCLOMETHICONE 6; DIMETHICONE/VINYL DIMETHICONE CROSSPOLYMER (SOFT PARTICLE); POLYGLYCERYL-4 ISOSTEARATE; CETYL PEG/PPG-10/1 DIMETHICONE (HLB 2); SILICA DIMETHYL SILYLATE; TRIETHOXYCAPRYLYLSILANE; PHENOXYETHANOL; ETHYLHEXYLGLYCERIN; BUTYLENE GLYCOL; HEXYLENE GLYCOL; MICA; BROWN IRON OXIDE

Drug Facts

Active Ingredients:

Zinc Oxide - 6.0%

Titanium Dioxide - 4.5%

Purpose:

Sunscreen

Uses:

- Helps prevent sunburn.
- If used as directed with other sun protection measures, decreases the risk of skin cancer and early skin aging caused by the sun.

Warning:

- For external use only.

Do not use:

- On damaged or broken skin.

When using this products:

- Keep out of eyes.
- Rinse with water to remove.

Stop use and ask a doctor:

- If rash occurs.

Keep out of reach of children:

- If swallowed, get medical help or contact a Poison Control Center right away.

DOSAGE AND ADMINISTRATION

For Sunscreen use:

- Apply liberally 15 minutes before sun exposer.
- Use a water resistant sunscreen if swimming or sweating.
- Reapply at least every 2 hours.
- Children under 6 months: ask a doctor.
- Sun protection measures.Spending time in the sun increase your risk of skin cancer and early skin aging. To decrease the risk, regularly use a sunscreen with a Broad Spectrum SPF of 15 or higher and other sun protection measures including:
- limit time in the sun, especially from 10 a.m. - 2 p.m.
- wear long sleeve shirts, pants, hats and sunglasses.

OTHER SAFETY INFORMATION

Protect this product from excessive heat and direct sun.

QUESTIONS

Call toll free 1-877-263-1625.

INACTIVE INGREDIENT

Inactive Ingredients: Water, Cyclopentasiloxane, C12-15 Alkyl Benzoate, Dimethicone Ployglyceryl-3, Polydimethylsiloxyethyl Dimethicone, Dimethicone/PEG -10/15 Crosspolymer, Stearic Acid, Aluminum Hydroxide, Sodium Chloride, Glycerin, Magnolia officinallis Bark Extract, Ectoin, Caprylyl Glycol, Teprenone, Sodium Hyaluronate, Vitis Vinifera, (Grape) seed extract, Citrus LLimon (Lemon) Peel Oil, Citrus Aurantium Dulcis (Orange) Peel Oil, Citrus Aurantium Bargamia (Bergamot) Fruit Oil, Pelargonium Graviolens Flower Oil, Cymbopogon Martini Oil, Citrus Aurantifolia (Lime) Oil, Juniperus Mexicana Oil, Citral, Anisaldehyde, Tagetes Minuta Flower Oil, Michelia Campaca Flower Oil, Tetrahexyldecyl Ascorbate, Ergothioneine, Tocopheryl Acetate, Tocopherol, Maltodextrin, Lecithin, Ethylhexyl Palmitate Caprylyc/Capric Triglyceride, PEG/PPG-18/18 Dimethicone, Polyglycerin-3 Crosspolymer, Hexyl Laurate, Cyclohexasiloxane, Triethoxysilylethyl Polydimethylsiloxyethyl Hexyl Dimethicone, Dimethicone/Venyl Dimethicone Crosspolymer, Polyglyceryl-4 Isostearate, Cetyl PEG/PPG-10/1 Dimethicone, Silica Dimethyl Sylilate, Triethoxycaprylylsilane, Phenoxyethanol, Ethylhexylglycerin, Butylene Glycol, Hexylene Glycol Fragrance, Mica, Silaca, May contains: Iron Oxide, Titanium Dioxide.

PACKAGE LABEL

Dist. by EVER LLC

Brisbane, CA 94005

Made in USA.